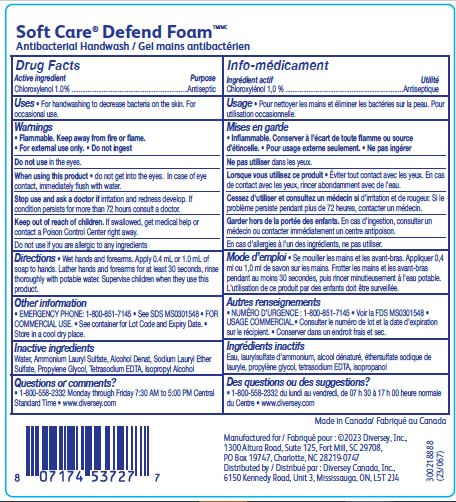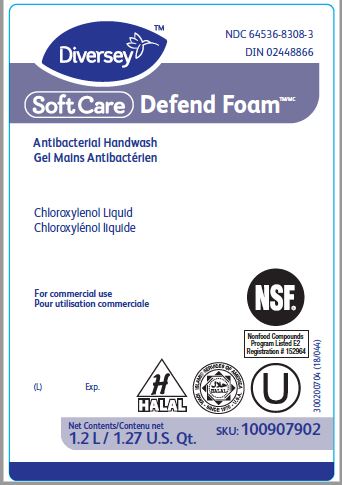 DRUG LABEL: Soft Care Defend Foam Antibacterial Handwash
NDC: 64536-8308 | Form: SOLUTION
Manufacturer: Diversey, Inc.
Category: otc | Type: HUMAN OTC DRUG LABEL
Date: 20231214

ACTIVE INGREDIENTS: CHLOROXYLENOL 1 g/100 mL
INACTIVE INGREDIENTS: ALCOHOL; PROPYLENE GLYCOL; AMMONIUM LAURYL SULFATE; ISOPROPYL ALCOHOL; EDETATE SODIUM; SODIUM LAURETH-3 SULFATE; WATER

Drug Facts NDC 64536-8308

Active ingredient

Chloroxylenol 1.0%

Purpose

Antiseptic

Uses

For handwashing to decrease bacteria on the skin.

For occasional use.

Warnings

Flammable. Keep away from fire or flame.

For external use only.

Do not ingest.

Do not use in the eyes.

When using this product do not get into eyes.

In case of eye contact, immediately flush with water.

Stop use and ask a doctor if irritation and redness develop.

If condition persists for more than 72 hours consult a doctor.

Keep out of reach of children.

If swallowed, get medical help or contact a Poison Control center right away.

Do not use if you are allergic to any ingredients

Directions

Wet hands and forearms.

Apply 0.4 mL or 1.0 mL of soap to hands.

Lather hands and forearms for at least 30 seconds, rinse thoroughly with potable water.

Supervise children when they use this product.

Other information

EMERGENCY PHONE: 1-800-851-7145

See SDS MS0301548

FOR COMMERCIAL USE.

See container for Lot Code and Expiry Date.

Store in a cool dry place.

Inactive ingredients

Water, Ammonium Lauryl Sulfate, Alcohol Denat, Sodium Lauryl Ether Sulfate, Propylene Glycol, Tetrasodium EDTA, Isopropyl Alcohol

Questions or comments?

1-800-558-2332 Monday through Friday 7:30 AM to 5:00 PM Central Standard Time

www.diversey.com

PACKAGE LABEL

NDC 64536-8308-3

DIN 02448866

Diversey

SoftCare Defend Foam

Antibacterial Handwash

Chloroxylenol Liquid

For commercial use

NSF

Nonfood Compounds

Program listed E2

Registration # 152964

(L) Exp.

U

Net Contents

1.2 L/ 1.27 U.S. Qt.

SKU: 100907902